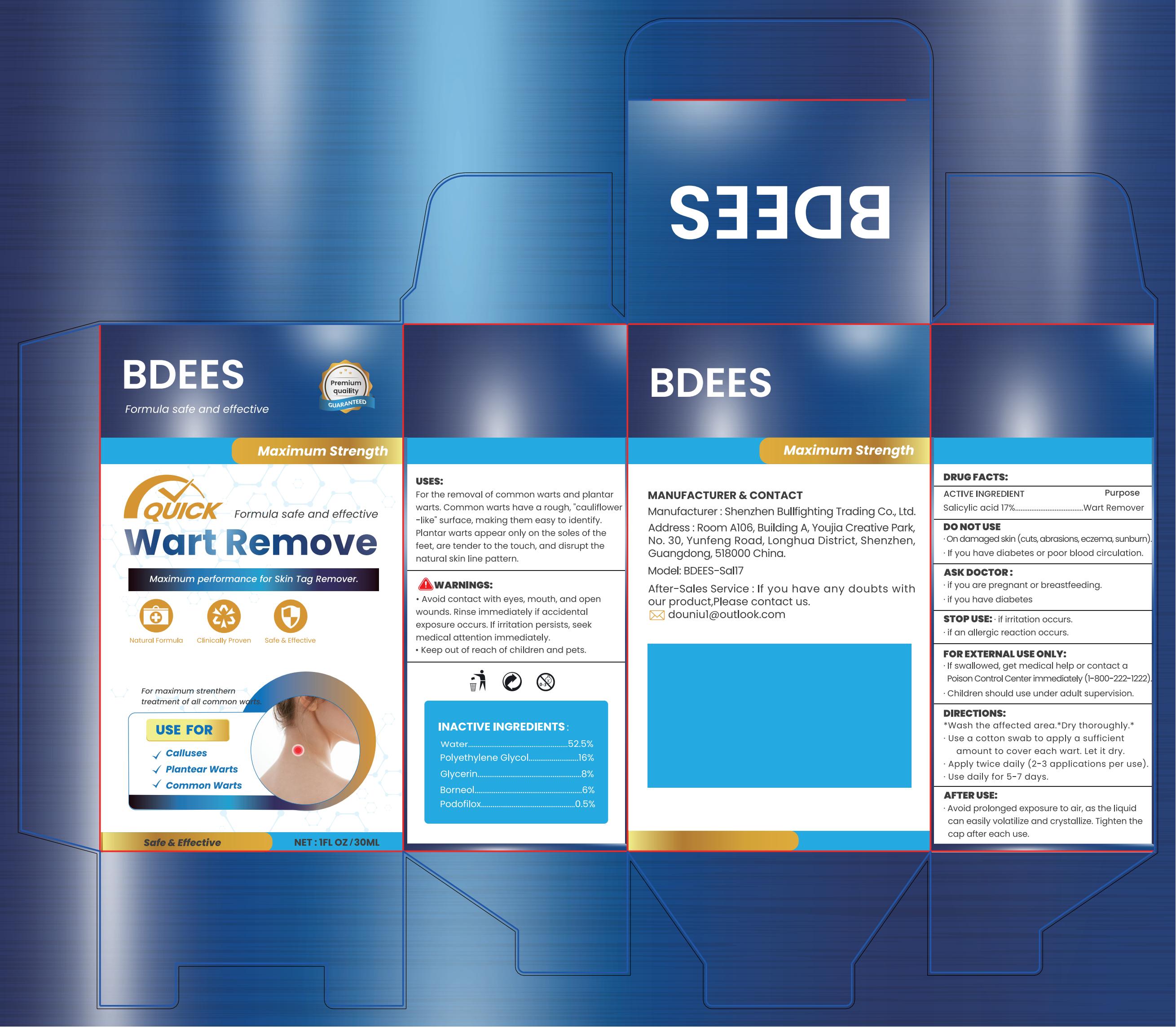 DRUG LABEL: Wart Remover
NDC: 85834-002 | Form: LIQUID
Manufacturer: Shenzhen Bullfighting Trading Co., Ltd.
Category: otc | Type: HUMAN OTC DRUG LABEL
Date: 20250629

ACTIVE INGREDIENTS: SALICYLIC ACID 17 g/100 mL
INACTIVE INGREDIENTS: WATER; POLYETHYLENE GLYCOL, UNSPECIFIED; GLYCERIN; PODOFILOX; BORNEOL

85834-002

Active Ingredient

Salicylic acid 17%

Purpose

Wart Remover

Use

For the removal of common warts and plantarwarts. Common warts have a rough, "cauliflowwer-like" surface, making them easy to identify.Plantar warts appear only on the soles of thefeet, are tender to the touch, and disrupt thenatural skin line pattern.

Warnings

Avoid contact with eyes, mouth, and open wounds. Rinse immediately if accidental exposure occurs. If irritation persists, seek
medical attention immediately.
• Keep out of reach of children and pets.

Do not use

On damaged skin (cuts, abrasions, eczema, sunburn).
If you have diabetes or poor blood circulation.

When Using

Skin discoloration may occur during or after use.

Stop Use

if irritation occurs. if an allergic reaction occurs.

Ask Doctor

if you are pregnant or breastfeeding.
if you have diabetes

Keep out of reach of children and pets.

If swallowed, get medical help or contact a Poison Control Center immediately (1-800-222-1222).
Children should use under adult supervision.

Directions

*Wash the affected area.*Dry thoroughly.*
Use a cotton swab to apply a sufficient amount to cover each wart. Let it dry.
Apply twice daily (2-3 applications per use).
Use daily for 5-7 days.

Other information

Avoid prolonged exposure to air, as the liquidcan easily volatilize and crystallize. Tighten thecap after each use.

Inactive ingredients

Water，Polyethylene Glycol，Glycerin，Borneol，Podofilox

Questions

Email：douniu1@outlook.com